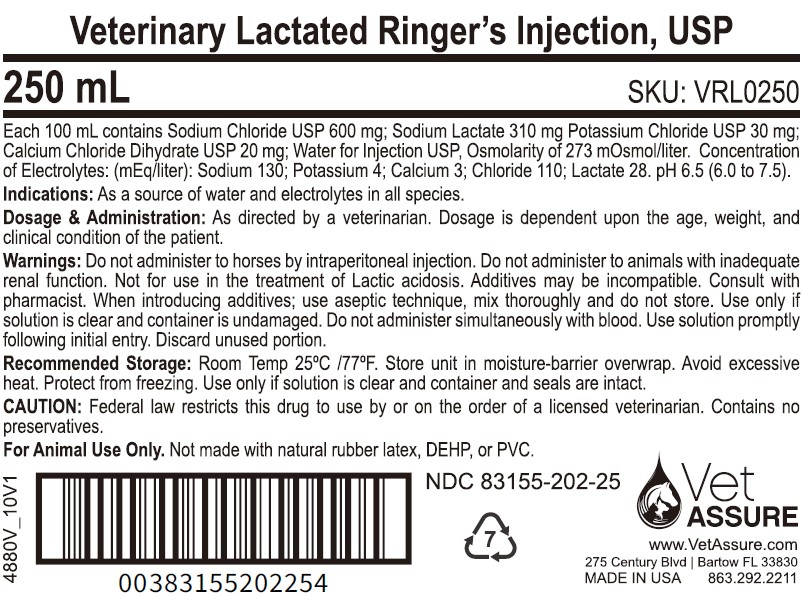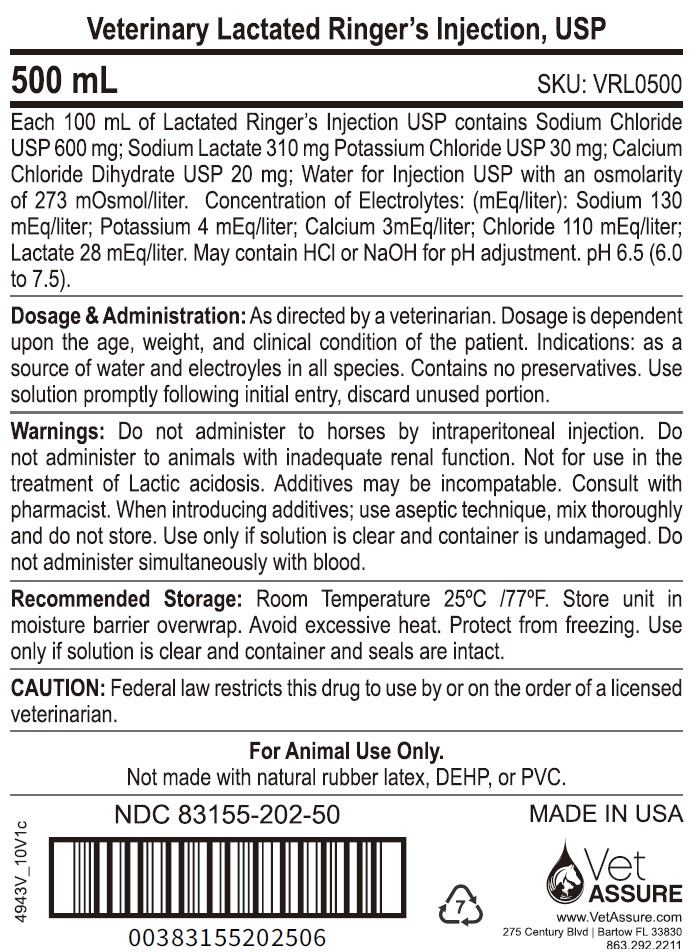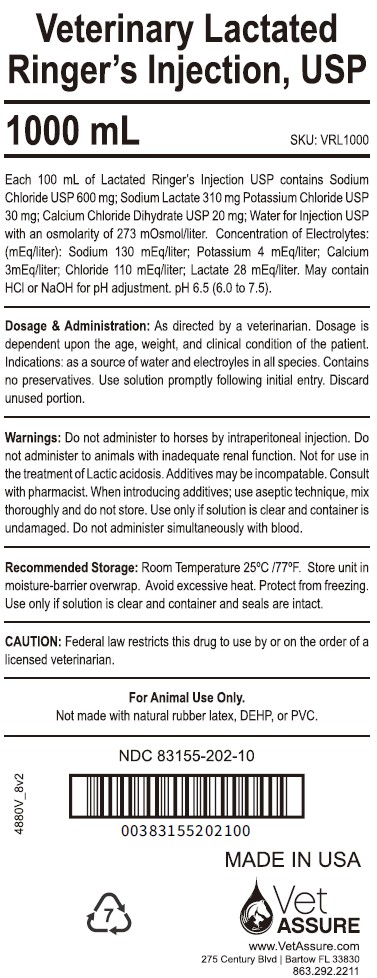 DRUG LABEL: Veterinary Lactated Ringers
NDC: 83155-202 | Form: INJECTION, SOLUTION
Manufacturer: Assure Infusions, Inc
Category: animal | Type: PRESCRIPTION ANIMAL DRUG LABEL
Date: 20250828

ACTIVE INGREDIENTS: sodium lactate 310 mg/100 mL; sodium chloride 600 mg/100 mL; potassium chloride 30 mg/100 mL; calcium chloride 20 mg/100 mL
INACTIVE INGREDIENTS: Water

For Animal Use Only

Description:

Veterinary Lactated Ringer's Injection, USP is a sterile, nonpyrogenic solution for fluid and electrolyte replenishment in single dose containers for parenteral administration. It contains no antimicrobial agents.

Table 1 Veterinary Lactated Ringer's Injection, USP
 | Composition (mg/100mL) |  |  |  |  |  | Ionic Concentration (mEq/L) |  |  |  |  | kcal/L
Size (mL) | Sodium Chloride, USP (NaCl) | Sodium Lactate, USP (C3H5NaO3) | Potassium Chloride, USP (KCl) | Calcium Chloride, USP (CaCl2∙ 2H2O) | Osmolarity (mOsmol/L) (Calculated) | pH | Sodium | Potassium | Calcium | Chloride | Lactate | Caloric Content
250 | 600 | 310 | 30 | 20 | 273 | 6.5 (6.0 to 7.5) | 130 | 4 | 2.7 | 109 | 28 | 9
500 | 600 | 310 | 30 | 20 | 273 | 6.5 (6.0 to 7.5) | 130 | 4 | 2.7 | 109 | 28 | 9
1000 | 600 | 310 | 30 | 20 | 273 | 6.5 (6.0 to 7.5) | 130 | 4 | 2.7 | 109 | 28 | 9
 | 600 | 310 | 30 | 20 | 273 | 6.5 (6.0 to 7.5) | 130 | 4 | 2.7 | 109 | 28 | 9

Clinical Pharmacology:

Veterinary Lactated Ringer's Injection, USP has value as a source of water and electrolytes. It is capable of inducing diuresis depending on the clinical condition of the patient.

Veterinary Lactated Ringer's Injection, USP produces a metabolic alkalinizing effect. Lactate ions are metabolized ultimately to carbon dioxide and water, which requires the consumption of hydrogen cations.

Indications and Usage:

Veterinary Lactated Ringer's Injection, USP is indicated as a source of water and electrolytes or as an alkalinizing agent.

Warnings:

Do not administer to horses by intraperitoneal injection.

Veterinary Lactated Ringer's Injection, USP should be used with great care, if at all, in patients with congestive heart failure, severe renal insufficiency, and in clinical states in which there exists edema with sodium retention.

Veterinary Lactated Ringer's Injection, USP should be used with great care, if at all, in patients with hyperkalemia, severe renal failure, and in conditions in which potassium retention is present.

Veterinary Lactated Ringer's Injection, USP should be used with great care in patients with metabolic or respiratory alkalosis. The administration of lactate ions should be done with great care in those conditions in which there is an increased level or an impaired utilization of these ions, such as severe hepatic insufficiency.

Veterinary Lactated Ringer's Injection, USP should not be administered simultaneously with blood through the same administration set because of the likelihood of coagulation.

The parenteral administration of Veterinary Lactated Ringer's Injection, USP can cause fluid and/or solute overloading resulting in dilution of serum electrolyte concentrations, overhydration, congested states, or pulmonary edema. The risk of dilutional states is inversely proportional to the electrolyte concentrations of the injections. The risk of solute overload causing congested states with peripheral and pulmonary edema is directly proportional to the electrolyte concentrations of the injections.

In patients with diminished renal function, administration of Veterinary Lactated Ringer's Injection, USP may result in sodium or potassium retention.

Veterinary Lactated Ringer's Injection, USP is not for use in the treatment of lactic acidosis.

Adverse Reactions:

Reactions which may occur because of the solution or the technique of administration include febrile response, infection at the site of injection, venous thrombosis or phlebitis extending from the site of injection, extravasation, and hypervolemia. If an adverse reaction does occur, discontinue the infusion, evaluate the patient, institute appropriate therapeutic countermeasures, and save the remainder of the fluid for examination if deemed necessary.

Precautions:

Clinical evaluation and periodic laboratory determinations are necessary to monitor changes in fluid balance, electrolyte concentrations, and acid base balance during prolonged parenteral therapy or whenever the condition of the patient warrants such evaluation. Veterinary Lactated Ringer's Injection, USP must be used with caution. Excess administration may result in metabolic alkalosis. Caution must be exercised in the administration of Veterinary Lactated Ringer's Injection, USP to patients receiving corticosteroids or corticotropin. Do not administer unless solution is clear and seal is intact.

Dosage and Administration:

As directed by a veterinarian. Dosage is dependent upon the age, weight and clinical condition of the patient, as well as laboratory determinations. Parenteral drug products should be inspected visually for particulate matter and discoloration prior to administration whenever solution and container permit.

All solutions for injection contained in plastic containers are intended for administration using sterile equipment and aseptic technique. Additives may be incompatible. Complete information is not available. Those additives known to be incompatible should not be used. Consult with pharmacist, if available. If, in the informed judgment of the veterinarian, it is deemed advisable to introduce additives, use aseptic technique. Mix thoroughly when additives have been introduced. Do not store solutions containing additives. Discard unused portion.

Overdosage:

In an event of overhydration or solute overload, re-evaluate the patient and institute appropriate corrective measures. See Warnings, Adverse Reactions and Precautions.

How Supplied:

Veterinary Lactated Ringer's Injection, USP is supplied in plastic bags as follows:

The plastic container is fabricated from a multi-layer, Polyolefin/Styrene-block copolymer film. The amount of water that can permeate from inside the container into the overwrap is insufficient to affect the solution significantly.

STORAGE AND HANDLING

STORAGE: Exposure of pharmaceutical products to heat should be minimized. Avoid excessive heat. It is recommended the product be stored in the moisture barrier overwrap at room temperature (25°C/77°F); brief exposure up to (40°C/104°F) does not adversely affect the product.

Directions for use of plastic container

To Open

Tear overwrap down side at slit and remove solution bag. Some opacity of the plastic due to moisture absorption during the sterilization process may be observed. This is normal and does not affect the solution quality or safety. The opacity will diminish gradually. Check for minute leaks by squeezing inner bag firmly. If leaks are found, discard solution as sterility may be impaired. If supplemental medication is desired, follow directions below.

Preparation for Administration

1. Suspend container from eyelet support.
2. Remove protector from outlet port at bottom of container.
3. Attach administration set. Refer to complete directions accompanying set.

To Add Medication

WARNING: Additives may be incompatible.

To add medication before solution administration

1. Prepare medication site.
2. Using syringe with 19 to 22 gauge needle, puncture resealable medication port and inject.
3. Mix solution and medication thoroughly. For high density medication such as potassium chloride, squeeze ports while ports are upright and mix thoroughly.

To add medication during solution administration

1. Close clamp on the administration set to stop the flow to the patient.
2. Prepare medication site.
3. Using syringe with 19 to 22 gauge needle, puncture resealable medication port and inject.
4. Remove container from IV pole and/or turn to an upright position.
5. Evacuate both ports by squeezing them while container is in the upright position.
6. Mix solution and medication thoroughly.
7. Return container to in-use position and continue administration.